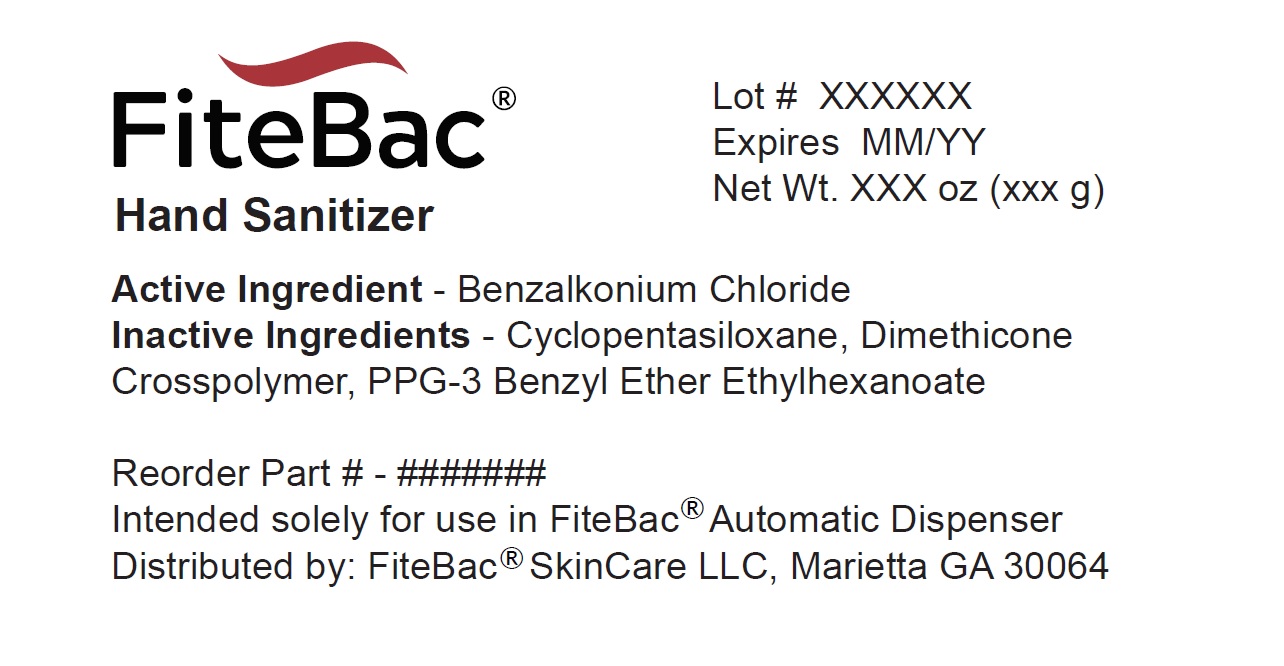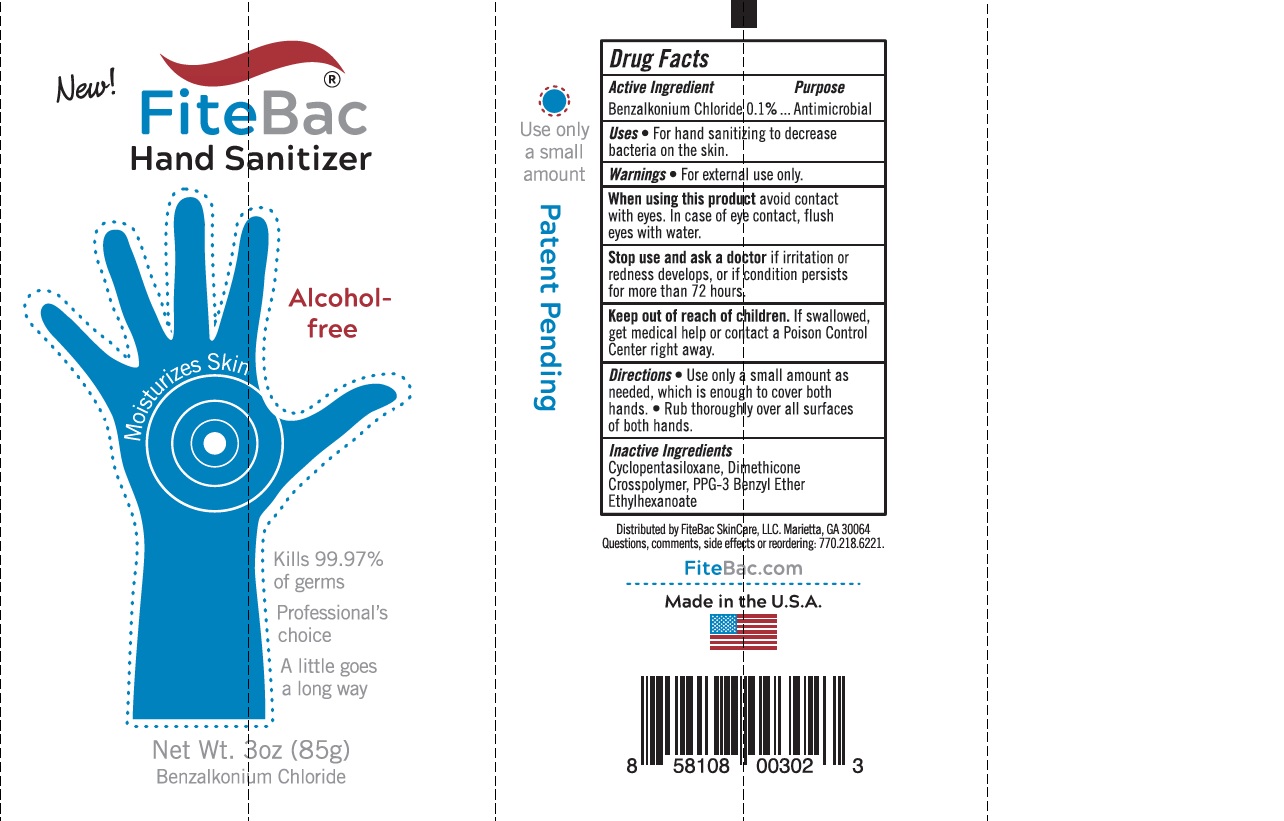 DRUG LABEL: FiteBac Hand Sanitizer
NDC: 13136-002 | Form: GEL
Manufacturer: FiteBac SkinCare, LLC
Category: otc | Type: HUMAN OTC DRUG LABEL
Date: 20201226

ACTIVE INGREDIENTS: BENZALKONIUM CHLORIDE 1 mg/1 g
INACTIVE INGREDIENTS: DIMETHICONE CROSSPOLYMER (450000 MPA.S AT 12% IN CYCLOPENTASILOXANE); PPG-3 BENZYL ETHER ETHYLHEXANOATE

FiteBac Hand Sanitizer

Drug Facts

Active ingredient

Benzalkonium Chloride 0.1%

Purpose

Antimicrobial

Uses

- For hand sanitizing to decrease bacteria on the skin

Warnings

For external use only

When using this product avoid contact with eyes. In case of eye contact, flush eyes with water.

Stop use and ask a doctor if irritation or redness develops, or if condition persists for more than 72 hours.

Keep out of reach of children. If swallowed, get medical help or contact a Poison Control Center right away.

Directions

- Use only a small, pea-sized amount as needed, which is enough to cover both your hands.
- Rub thoroughly over all surfaces of both hands

STORAGE AND HANDLING

- Not intended to provide ongoing protection against new germ exposure

Inactive ingredients

Cyclopentasiloxane, Dimethicone Crosspolymer, PPG-3 Benzyl Ether Ethylhexanoate

Questions, comments, side effects or reordering

770-218-6221

Distributed by FiteBac SkinCare, LLC, Marietta, Georgia 30064

PRINCIPAL DISPLAY PANEL

Tube Display